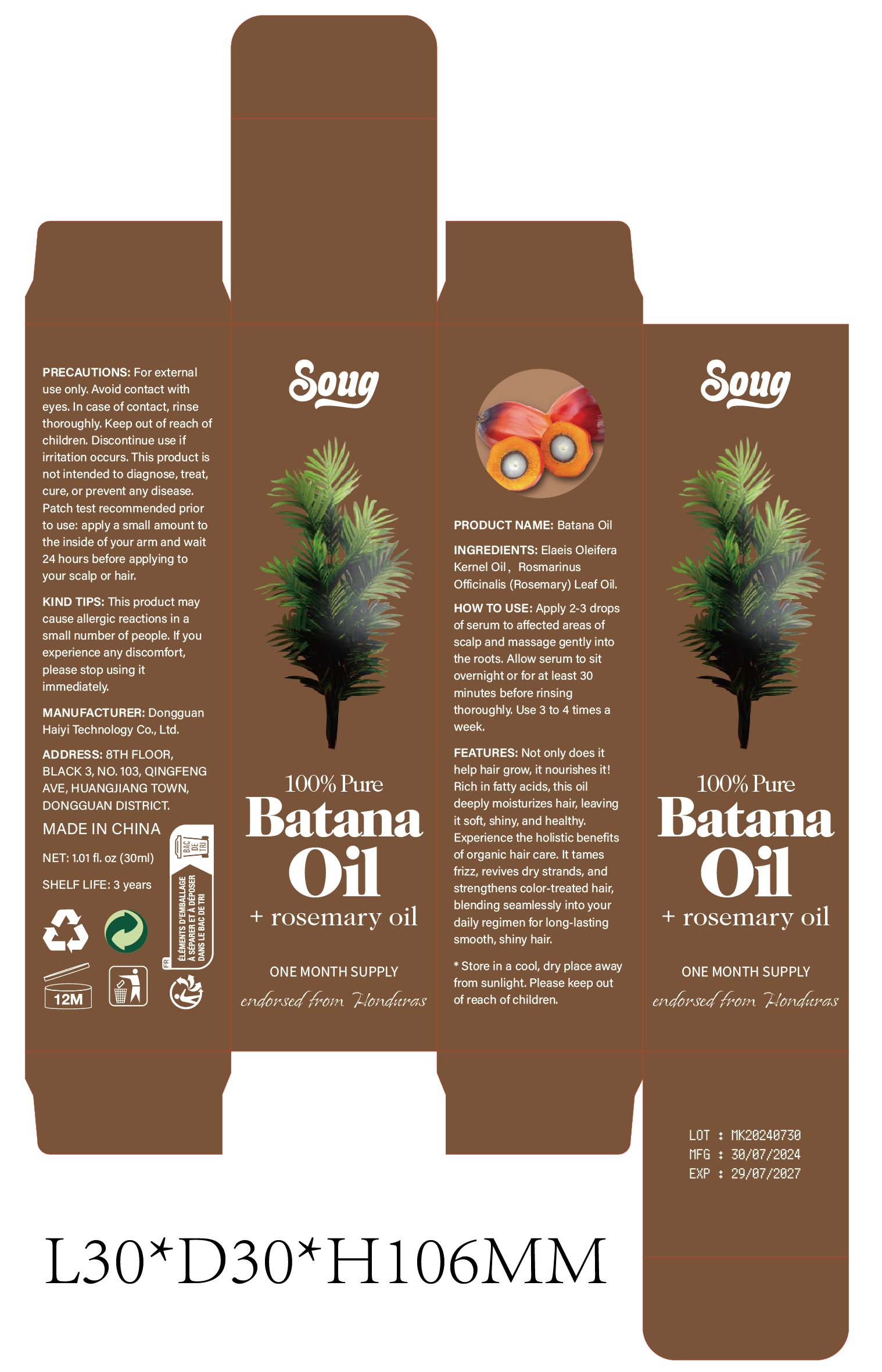 DRUG LABEL: Batana Oil
NDC: 84732-041 | Form: OIL
Manufacturer: Dongguan Haiyi Technology Co.,Ltd.
Category: otc | Type: HUMAN OTC DRUG LABEL
Date: 20241013

ACTIVE INGREDIENTS: ELAEIS OLEIFERA SEED OIL 1 mg/100 mL
INACTIVE INGREDIENTS: ROSEMARY OIL

Active ingredient

Elaeis Oleifera Kernel Oil

Inactive ingredient

Rosmarinus Officinalis (Rosemary) Leaf OiL

Purpose section

Not only does ithelp hair grow, it nourishes it!Rich in fatty acids, this oildeeply moisturizes hair, leavingit soft, shiny, and healthy.Experience the holistic benefitsof organic hair care. lt tamesfrizz, revives dry strands, andstrengthens color-treated hair,blending seamlessly into yourdaily regimen for long-lastingsmooth, shiny hair.

Warning

For externaluse only. Avoid contact witheyes. In case of contact, rinsethoroughly. keep out of reach of children. Discontinue use if irritation occurs. This product isnot intended to diagnose, treat,cure, or prevent any disease.Patch test recommended priorto use: apply a small amount to the inside of your arm and wait 24 hours before applying toyour scalp or hair.

stop use

This product may cause allergic reactions in asmall number of people.
lf you experience any discomfort,please stop using it immediately.

not use

Not suitable for use by children, pregnantor breast feeding people.

OUT OF CHILDREN

KEEP THE PRODUCT OUT OF REACH OF CHILDREN to

HOW TO USE

Apply 2-3 dropsof serum to affected areas of scalp and massage gently intothe roots. Allow serum to sitovernight or for at least 30 minutes before rinsing thoroughly.

Dosage

Use 3 to 4 times a week.